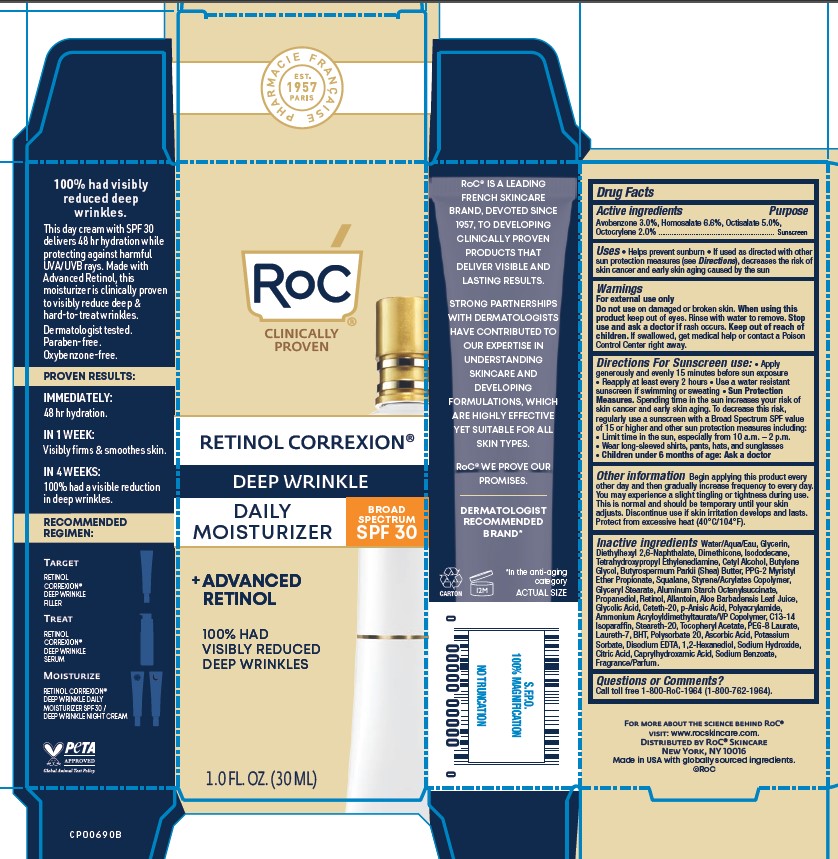 DRUG LABEL: RoC Retinol Correxion Wrinkle Correct Daily Moisturizer SPF 30
NDC: 73496-009 | Form: LOTION
Manufacturer: RoC Skincare
Category: otc | Type: HUMAN OTC DRUG LABEL
Date: 20251201

ACTIVE INGREDIENTS: OCTOCRYLENE 2 mg/100 mL; AVOBENZONE 3 mg/100 mL; HOMOSALATE 6.6 mg/100 mL; OCTISALATE 5 mg/100 mL
INACTIVE INGREDIENTS: C13-14 ISOPARAFFIN; ALPHA-TOCOPHEROL ACETATE; BHT; SODIUM HYDROXIDE; CAPRYLHYDROXAMIC ACID; SODIUM BENZOATE; PPG-2 MYRISTYL ETHER PROPIONATE; P-ANISIC ACID; STEARETH-20; ISODODECANE; BUTYLENE GLYCOL; WATER; GLYCERIN; PEG-8 LAURATE; ASCORBIC ACID; CITRIC ACID; LAURETH-7; ALUMINUM STARCH OCTENYLSUCCINATE; GLYCOLIC ACID; AMMONIUM ACRYLOYLDIMETHYLTAURATE/VP COPOLYMER; EDETATE DISODIUM; TETRAHYDROXYPROPYL ETHYLENEDIAMINE; POLYSORBATE 20; POTASSIUM SORBATE; CETETH-20; DIMETHICONE; DIETHYLHEXYL 2,6-NAPHTHALATE; ALOE BARBADENSIS LEAF JUICE; 1,2-HEXANEDIOL; SHEA BUTTER; CETYL ALCOHOL; POLYACRYLAMIDE (10000 MW); SQUALANE; STYRENE/ACRYLAMIDE COPOLYMER (MW 500000); GLYCERYL STEARATE; PROPANEDIOL; RETINOL; ALLANTOIN

RoC Retinol Correxion Wrinkle Correct Daily Moisturizer SPF 30

Active ingredients

Active ingredients Purpose

Avobenzone 3.0%, Homosalate 6.6%, Octisalate 5.0%, Octocrylene 2.0% Sunscreen

Uses

Uses • Helps prevent sunburn • If used as directed with other sun protection measures (see Directions), decreases the risk of skin cancer and early skin aging caused by the sun

Purpose

Sunscreen

Warnings

For external use only
Do not use on damaged or broken skin. When using this product keep out of eyes. Rinse with water to remove. Stop use and ask a doctor if rash occurs. Keep out of reach of children. If swallowed, get medical help or contact a Poison Control Center right away.

Keep out of reach of children

Directions For Sunscreen use: • Apply generously and evenly 15 minutes before sun exposure • Reapply at least every 2 hours • Use a water resistant sunscreen if swimming or sweating • Sun Protection Measures. Spending time in the sun increases your risk of
skin cancer and early skin aging. To decrease this risk, regularly use a sunscreen with a Broad Spectrum SPF value of 15 or higher and other sun protection measures including:
• Limit time in the sun, especially from 10 a.m. – 2 p.m.
• Wear long-sleeved shirts, pants, hats, and sunglasses
• Children under 6 months of age: Ask a doctor

Other information

Other information Begin applying this product every other day and then gradually increase frequency to every day. You may experience a slight tingling or tightness during use. This is normal and should be temporary until your skin adjusts. Discontinue use if skin irritation develops and lasts. Protect from excessive heat (40°C/104°F).

Inactive ingredients

Inactive ingredients Water/Aqua/Eau, Glycerin, Diethylhexyl 2,6-Naphthalate, Dimethicone, Isododecane, Tetrahydroxypropyl Ethylenediamine, Cetyl Alcohol, Butylene Glycol, Butyrospermum Parkii (Shea) Butter, PPG-2 Myristyl Ether Propionate, Squalane, Styrene/Acrylates Copolymer, Glyceryl Stearate, Aluminum Starch Octenylsuccinate, Propanediol, Retinol, Allantoin, Aloe Barbadensis Leaf Juice, Glycolic Acid, Ceteth-20, p-Anisic Acid, Polyacrylamide, Ammonium Acryloyldimethyltaurate/VP Copolymer, C13-14 Isoparaffin, Steareth-20, Tocopheryl Acetate, PEG-8 Laurate, Laureth-7, BHT, Polysorbate 20, Ascorbic Acid, Potassium Sorbate, Disodium EDTA, 1,2-Hexanediol, Sodium Hydroxide, Citric Acid, Caprylhydroxamic Acid, Sodium Benzoate, Fragrance/Parfum.

Questions or Comments?

Call toll free 1-800-RoC-1964 (1-800-762-1964).